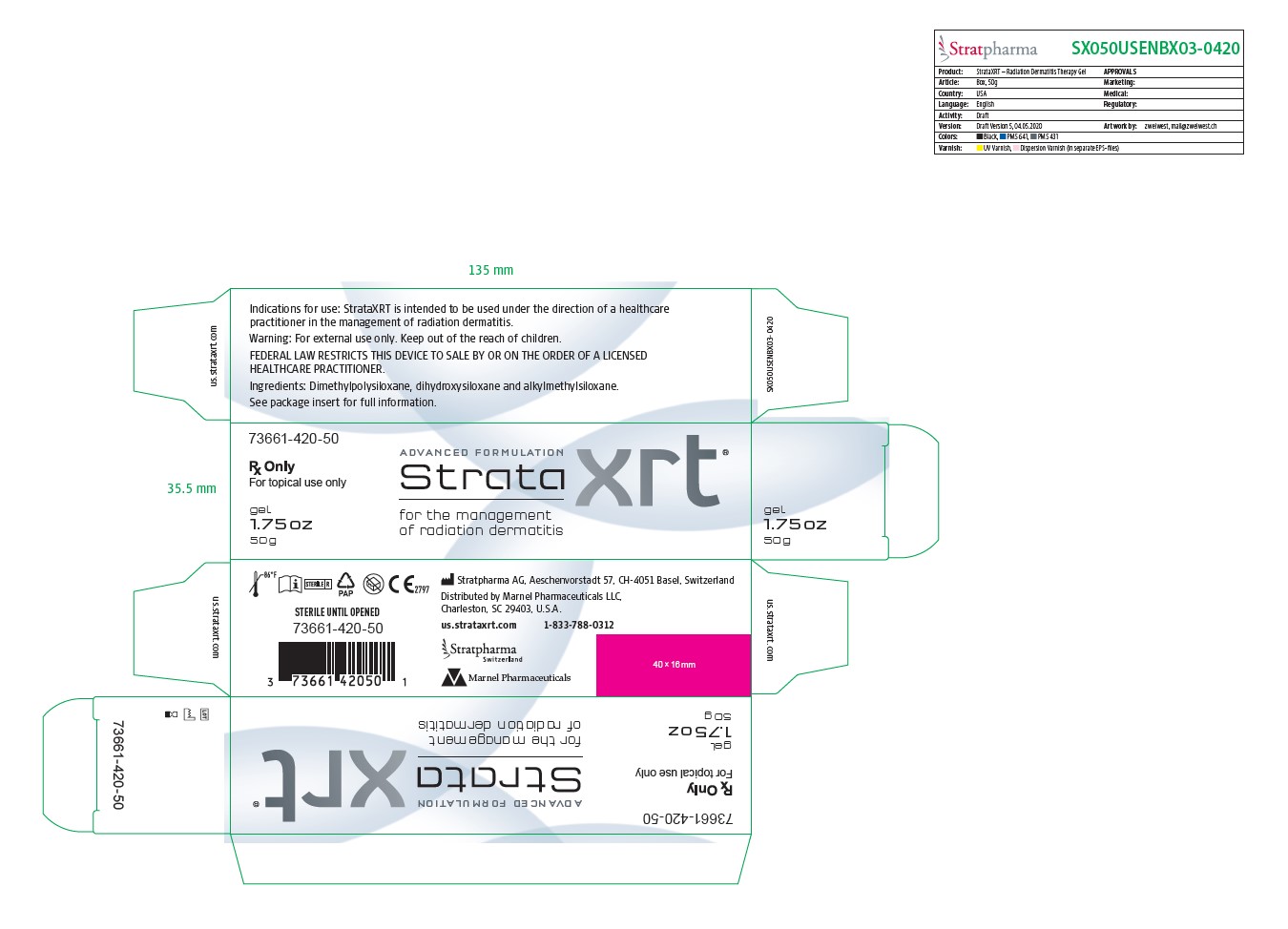 DRUG LABEL: STRATAXRT
NDC: 73661-420
Manufacturer: Marnel Pharmaceuticals, Inc.
Category: other | Type: MEDICAL DEVICE
Date: 20200713
INACTIVE INGREDIENTS: DIMETHICONE; DIMETHICONOL (2000 CST); CAPRYLYL TRISILOXANE

STRATAXRT

WARNINGS AND PRECAUTIONS

Rx Only

For Topical Use Only

Federal Law restricts this device to sale by or on the order of a licensed healthcare practitioner.

[EN] Description

StrataXRT is an occlusive, non-resorbable, self-drying and transparent gel.

When used as directed StrataXRT dries to form a protective layer that is gas permeable and waterproof which hydrates and protects compromised skin areas and superficial wounds from chemical and microbial invasion.

StrataXRT helps to promote a moist wound healing environment.

This moist wound healing environment promotes faster re-epithelialization* and reduces the skin's acute inflammatory response seen with both dry and moist desquamation.

In dry desquamation, StrataXRT protects the fragile epidermis and maintains the skin's integrity, preventing the outmost layers from excessive sloughing.

In moist desquamation, StrataXRT protects the dermal stroma from long-term deterioration and reduces the risk of infection.

StrataXRT is suitable for large surface areas and contoured skin like the breasts, face, back and pelvic area, as well as joints and hairy areas without the need for shaving.

INDICATIONS AND USAGE

Indication for use

StrataXRT is intended to be used under the direction of healthcare practitioners in the management of radiation dermatitis.

StrataXRT is indicated for use on all types of radiation dermatitis, toxic and compromised skin and superficial wounds resulting from radiation therapy.

StraXRT is indicated for the relief of dry, itching, flaking, peeling and irritated skin, as well as the symptomatic relief of pain, redness and heat sensation.

StrataXRT may be directly applied to superficial wounds and areas where skin integrity has been compromised.

StrataXRT is bacteriostatic and inert.

StrataXRT contains no alcohols, parabens or fragrances.

StrataXRT can be used with or without a seconday protective dressing.

StrataXRT is suitable for children and people with sensitive skin.

StrataXRT is intended for single patient use.

INDICATIONS AND USAGE

Directions for use

On the first use of 1.75 oz (50g) tubes, remove the cap, then the protective seal and close with the cap after use.

Ensure that the affected skin or superficial wound is clean and dry.

Gently pat dry as much excess exudate or wound fluid from the area as possible prior to gel application.

Apply a very thin layer of StrataXRT directly to the affected area and allow the gel to dry.

When applied correctly to exposed areas, StrataXRT should be dry in 5-6 minutes. If it takes longer to dry you have probably applied too much. Gently remove the excess with a clean tissue or gauze and allow the drying process to continue.

Once dry, StrataXRT may be convered by sunscreen, cosmetics and clothing.

StrataXRT should be applied once or twice daily to affected areas or as advised by your physician.

For best results, StrataXRT should be maintained in continuous contact with the skin (24 hours a day/7 days a week).

StrataXRTdoes not need to be removed prior to radiation therapy.

How much StrataXRT do I need?

StrataXRT gel is a unique formulation that requires substantially less product per application than typical creams or gels.

StrataXRT 1.75 oz (50g) is enough to treat an area of 6x12 inch (15x30 cm) twice a day for 30 days.

Warning

- For external use only.
- StrataXRT should not be placed in contact with the eyes.
- StrataXRT should not be applied over topical medications unless advised by your physician.
- StrataXRT may stain clothing if not completely dry. If staining occurs, dry cleaning should be able to remove it without damaging the fabric.
- For correct storage, please reclose the tube tightly with the cap.
- If irritation occurs, discontinue use and consult your physician.
- Keep out of reach of children.
- Do not use after the expiration (EXP) date printed on the tube. The expiration (EXP) date does not change once the tube has been opened.
- Do not use if the tube is damaged.

Contraindications:

Do not administer to patients with known hypersensitivity to the ingredients of this product.

STERILE UNTIL OPENED

Ingredients: Dimethylpolysiloxane, dihydroxysiloxane and alkylmethylsiloxane.

How supplied:

StrataXRT 1.75oz (50g) tube

Product identification code

73661-420-50